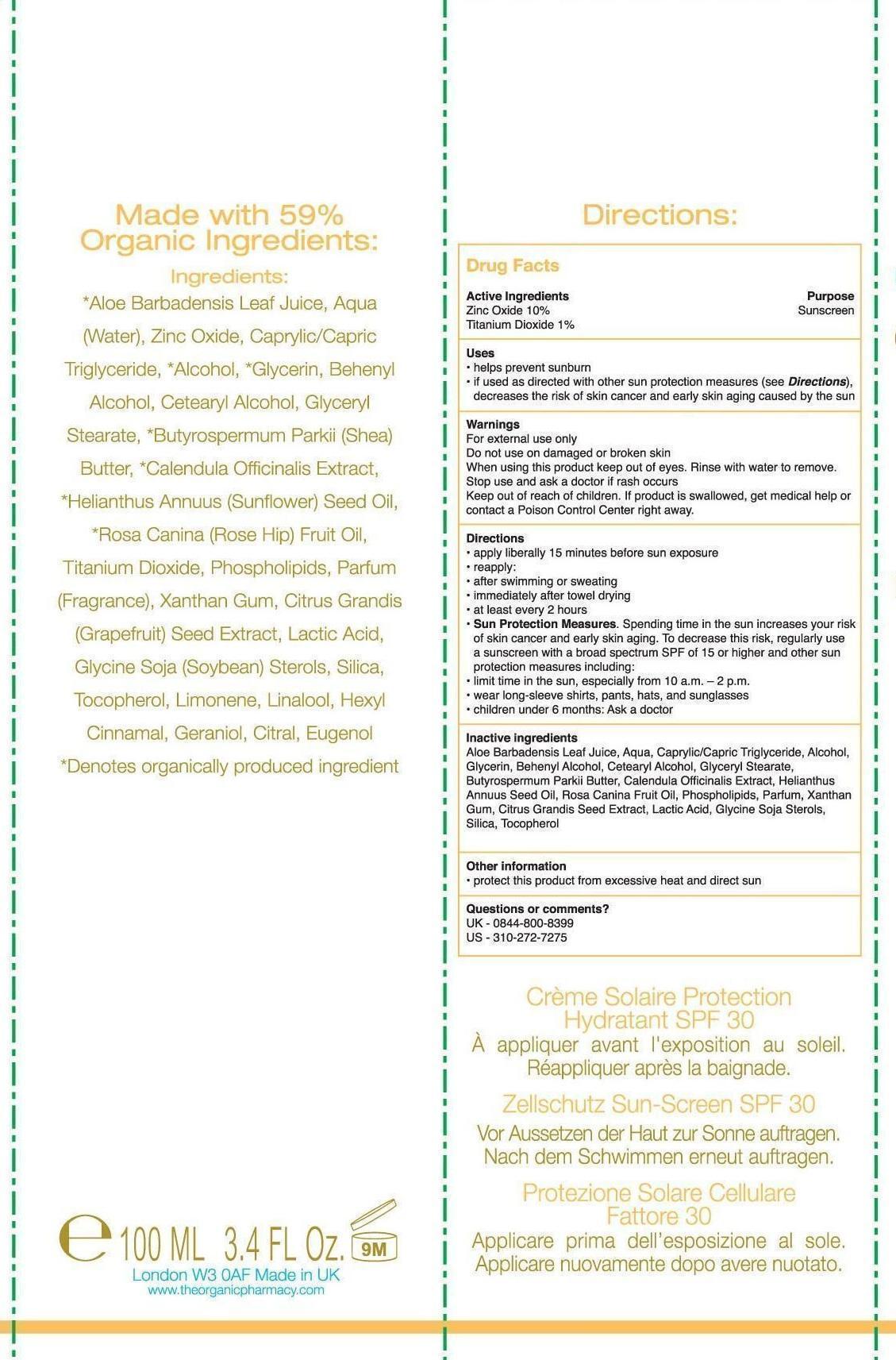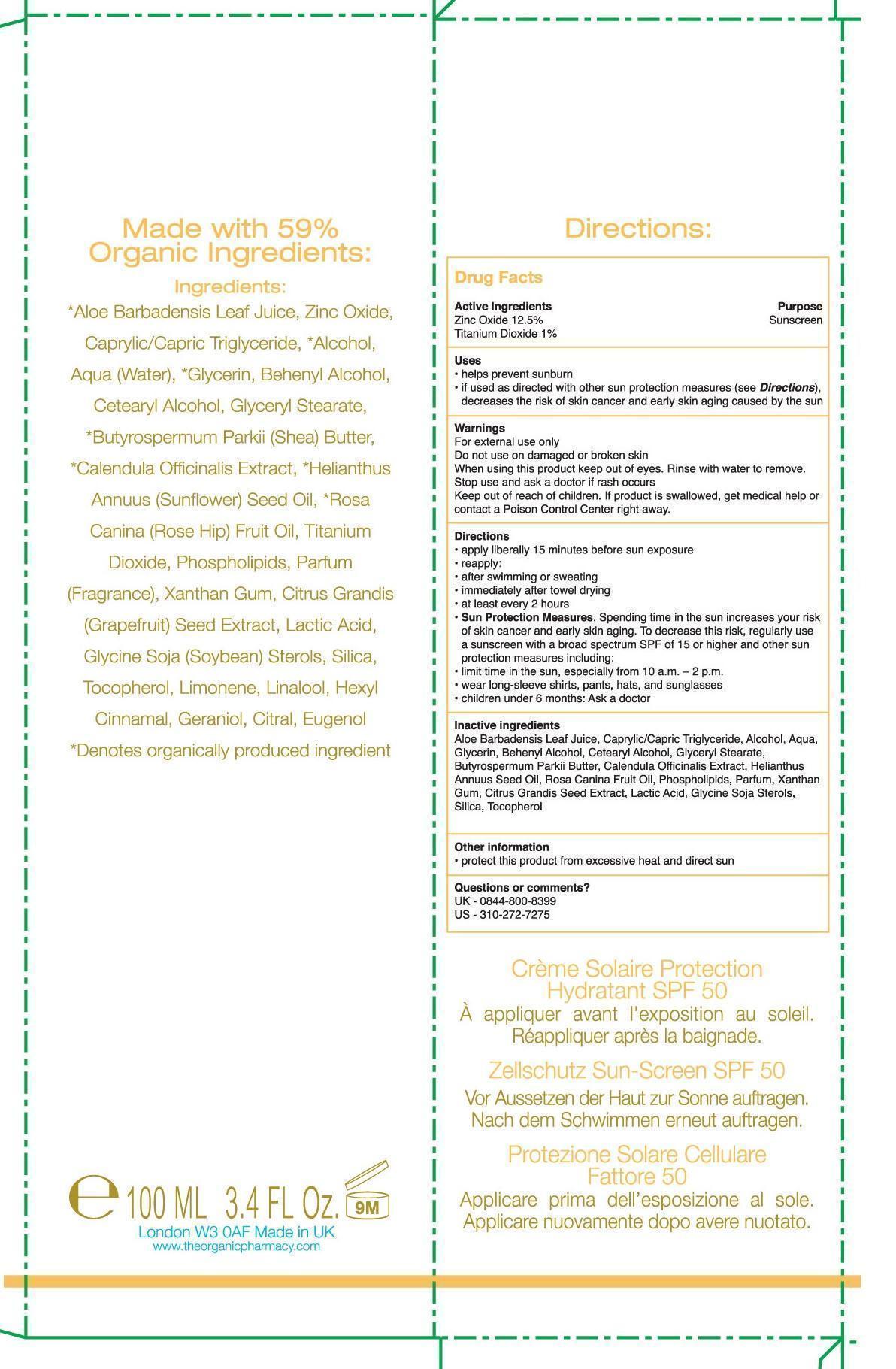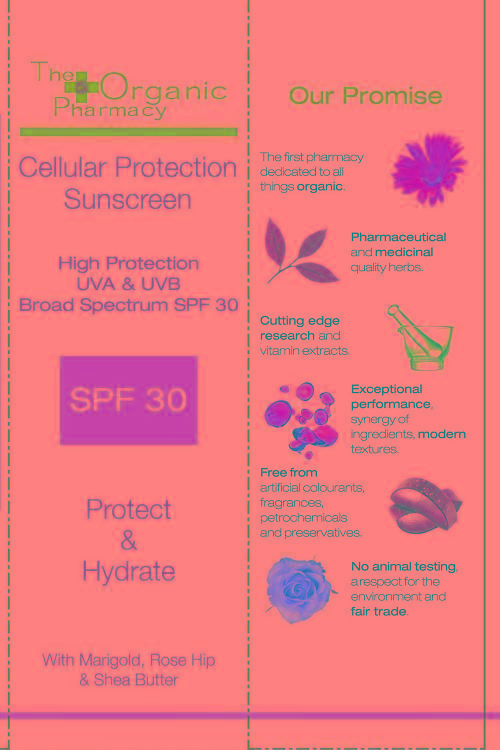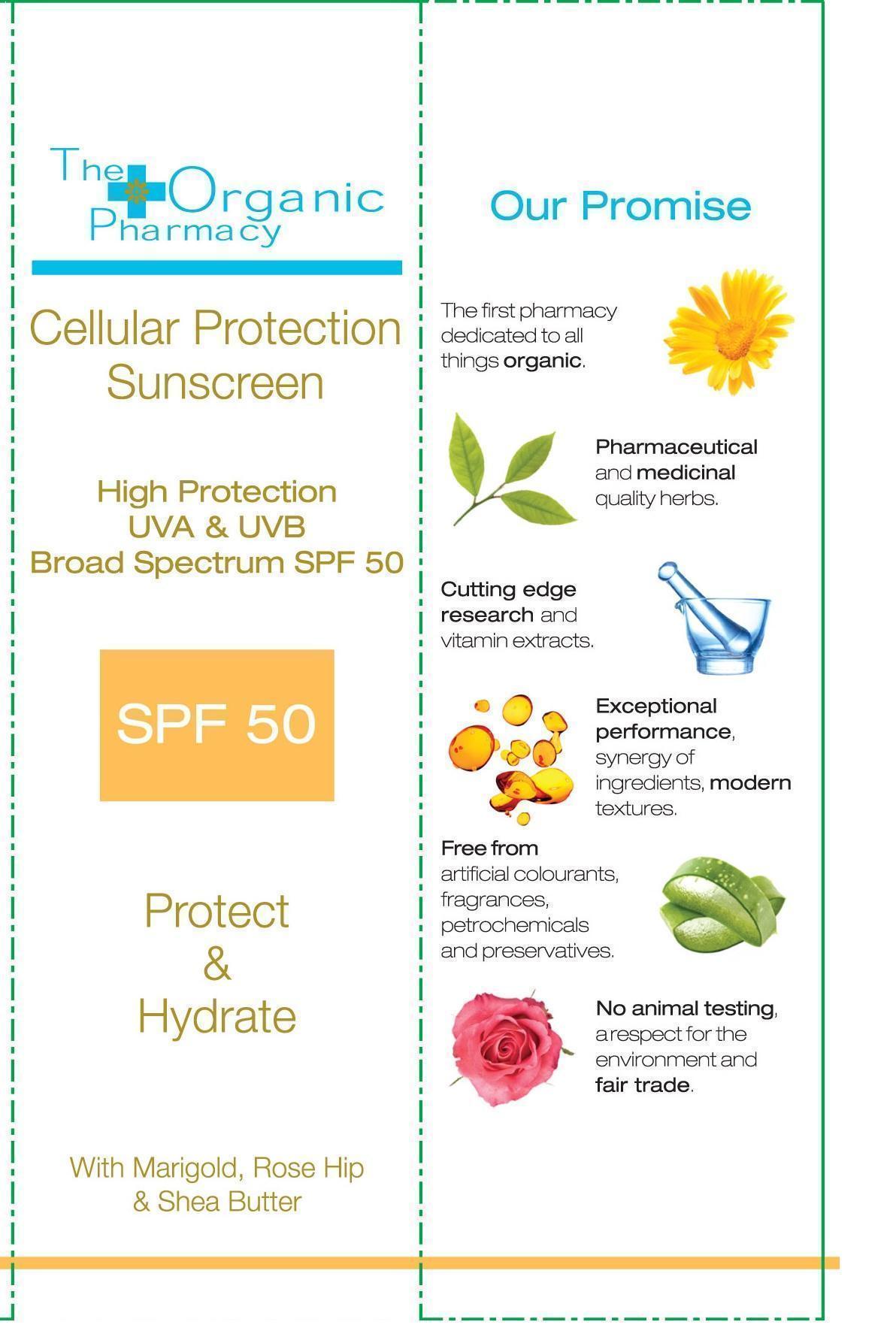 DRUG LABEL: The Organic Pharmacy Cellular Protection Sunscreen SPF 30
NDC: 69303-630 | Form: CREAM
Manufacturer: The organic pharmacy Limited
Category: otc | Type: HUMAN OTC DRUG LABEL
Date: 20180717

ACTIVE INGREDIENTS: TITANIUM DIOXIDE 1.0000 g/100 g; ZINC OXIDE 10.0000 g/100 g
INACTIVE INGREDIENTS: ALOE VERA LEAF 40.0000 g/100 g; WATER 12.7760 g/100 g; MEDIUM-CHAIN TRIGLYCERIDES 10.0000 g/100 g; ALCOHOL 10.0000 g/100 g; GLYCERIN 5.0760 g/100 g; DOCOSANOL 2.1150 g/100 g; CETOSTEARYL ALCOHOL 2.0000 g/100 g; GLYCERYL MONOSTEARATE 1.5750 g/100 g; SHEA BUTTER 1.0000 g/100 g; CALENDULA OFFICINALIS FLOWER 1.0000 g/100 g; SUNFLOWER OIL 1.0000 g/100 g; ROSA CANINA FRUIT OIL 1.0000 g/100 g; OMEGA-3 FATTY ACIDS 0.6750 g/100 g; XANTHAN GUM 0.2000 g/100 g; LACTIC ACID 0.1800 g/100 g; SOY STEROL 0.1350 g/100 g; CITRUS MAXIMA SEED 0.1180 g/100 g; SILICON DIOXIDE 0.1000 g/100 g; TOCOPHEROL 0.0500 g/100 g

The Organic Pharmacy-Cellular Protection Sunscreen SPF 30 & SPF 50

Carton.DrugFactsSPF50

Active ingredients

Zinc Oxide 12.5%

Titanium Dioxide 1%

Uses

- helps prevent sunburn
- if used as directed with other sun protection measures (see Directions), decreases the risk of skin cancer and early skin aging caused by the sun

Warnings

For external use only

Do not use on damaged or broken skin

When using this product keep out of eyes. Rinse with water to remove.

Stop use and ask a doctor if rash occurs.

Keep out of reach of children. If product is swallowed, get medical help or contact a Poison contorl Center right away.

Directions

- apply liberally 15 minutes before sun exposure
- reapply:
- after swimming or sweating
- immediately after towel drying
- at least every 2 hours
- Sun Protection Measures. Spending time in the sun increases your risk of skin cancer and early skin ageing. To decrease this risk, regularly use a sunscreen with a broad spectrum SPF of 15 or higher and other sun protection measures including:
- limit time in the sun, especially from 10 a.m. - 2 p.m.
- wear long sleeve shirts, pants, hats and sunglasses
- children under 6 months: Ask a doctor

Inactive ingredients

Aloe Barbadensis Leaf Juice, Caprylic/Capric Triglyceride, Alcohol, Aqua, Glycerin, Behenyl Alcohol, Cetearyl Alcohol, Glyceryl Stearate, Butyrospermum Parkii Butter, Calendula Officinalis Extract, Helianthus Annuus Seed Oil, Rosa Canina Fruit Oil, Phospholipids, Parfum , Xanthan Gum, Citrus Grandis Seed Extract, Lactic Acid, Glycine Soja Sterols, Silica, Tocopherol

Other information

- protect this product from excessive heat and direct sun

Questions or comments?

UK-0844-800-8399

US-310-272-7275

Carton.PrincipalDisplayPanelSPF50

Cellular Protection Sunscreen

High Protection UVA & UVB

Broad spectrum SPF 50

SPF50

Protect & Hydrate

With Marigold, Rose Hip & Shea Butter

CartonSPF30.DrugFacts

Active ingredients

Zinc Oxide 10 %

Titanium Dioxide 1%

Uses

- helps prevent sunburn
- if used as directed with other sun protection measures (see Directions), decreases the risk of skin cancer and early skin aging caused by the sun

Warnings

For external use only

Do not use on damaged or broken skin

When using this product keep out of eyes. Rinse with water to remove.

Stop use and ask a doctor if rash occurs.

Keep out of reach of children. If product is swallowed, get medical help or contact a Poison contorl Center right away.

Directions

- apply liberally 15 minutes before sun exposure
- reapply:
- after swimming or sweating
- immediately after towel drying
- at least every 2 hours
- Sun Protection Measures. Spending time in the sun increases your risk of skin cancer and early skin ageing. To decrease this risk, regularly use a sunscreen with a broad spectrum SPF of 15 or higher and other sun protection measures including:
- limit time in the sun, especially from 10 a.m. - 2 p.m.
- wear long sleeve shirts, pants, hats and sunglasses
- children under 6 months: Ask a doctor

Inactive ingredients

Aloe Barbadensis Leaf Juice, Aqua, Caprylic/Capric Triglyceride, Alcohol, Glycerin, Behenyl Alcohol, Cetearyl Alcohol, Glyceryl Stearate, Butyrospermum Parkii Butter, Calendula Officinalis Extract, Helianthus Annuus Seed Oil, Rosa Canina Fruit Oil, Phospholipids, Parfum , Xanthan Gum, Citrus Grandis Seed Extract, Lactic Acid, Glycine Soja Sterols, Silica, Tocopherol

Other information

- protect this product from excessive heat and direct sun

Questions or comments?

UK-0844-800-8399

US-310-272-7275

Carton.PrincipalDisplayPanelSPF30

Cellular Protection Sunscreen

High Protection UVA & UVB

Broad spectrum SPF 30

SPF30

Protect & Hydrate

With Marigold, Rose Hip & Shea Butter